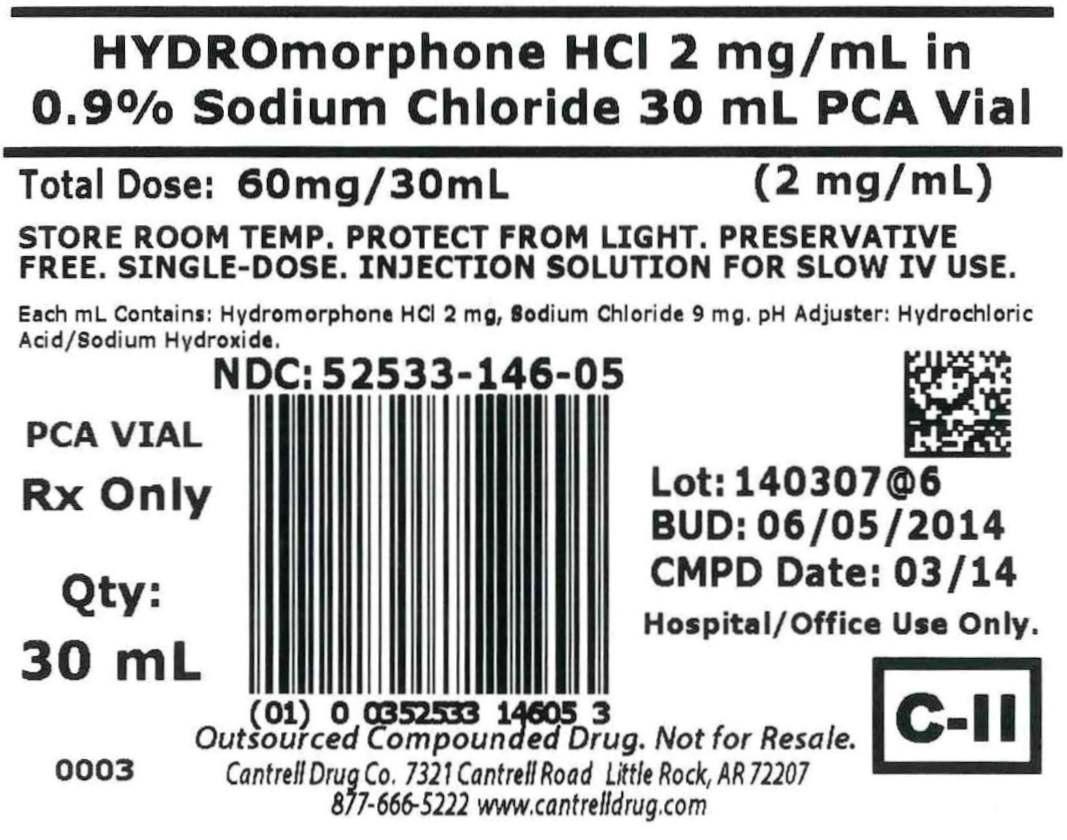 DRUG LABEL: Hydromorphone HCl
NDC: 52533-146 | Form: INJECTION, SOLUTION
Manufacturer: Cantrell Drug Company
Category: prescription | Type: HUMAN PRESCRIPTION DRUG LABEL
Date: 20140820
DEA Schedule: CII

ACTIVE INGREDIENTS: HYDROMORPHONE HYDROCHLORIDE 2 mg/1 mL
INACTIVE INGREDIENTS: Sodium Chloride 9 mg/1 mL; WATER

Hydromorphone HCl 2 mg/mL in 0.9% Sodium Chloride 30 mL PCA Vial